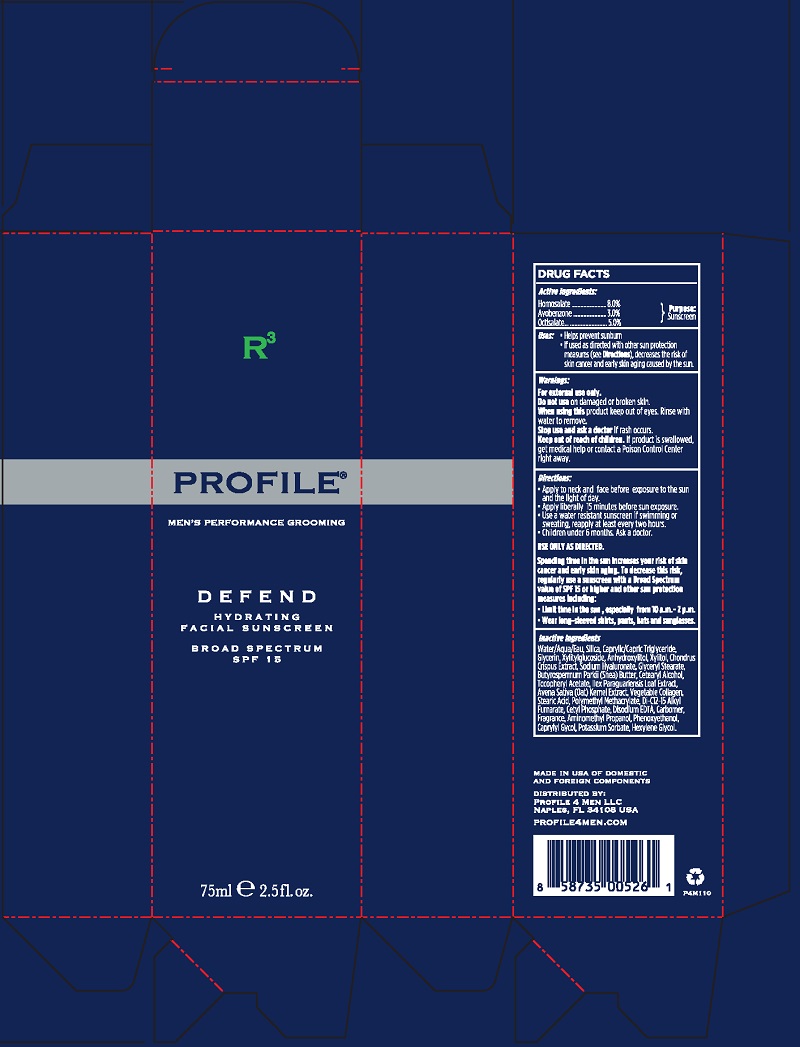 DRUG LABEL: Defend Hydrating Broad Spectrum SPF 15
NDC: 70384-100 | Form: CREAM
Manufacturer: Profile 4 Men LLC
Category: otc | Type: HUMAN OTC DRUG LABEL
Date: 20160418

ACTIVE INGREDIENTS: HOMOSALATE 6 mg/75 mL; AVOBENZONE 2.25 mg/75 mL; OCTISALATE 3.75 mg/75 mL
INACTIVE INGREDIENTS: WATER; SILICON DIOXIDE; CAPRYLIC/CAPRIC/LAURIC TRIGLYCERIDE; GLYCERIN; XYLITYLGLUCOSIDE; ANHYDROXYLITOL; XYLITOL; CHONDRUS CRISPUS; POLY(METHYL METHACRYLATE; 450000 MW); GLYCERYL STEARATE SE; SHEA BUTTER; STEARYL ALCOHOL; ALPHA-TOCOPHEROL ACETATE; ILEX PARAGUARIENSIS LEAF; AVENA SATIVA WHOLE; SOY PROTEIN; STEARIC ACID; METHACRYLATE/METHOXY PEG-10 MALEATE/STYRENE COPOLYMER; DI-C12-15 ALKYL FUMARATE; CETYL PHOSPHATE; EDETIC ACID; CARBOMER 934; AMINOMETHYLPROPANOL; PHENOXYETHANOL; CAPRYLYL GLYCOL; POTASSIUM SORBATE; HEXYLENE GLYCOL

Defend Hydrating Broad Spectrum SPF 15

Active Ingredients:

Homosolate..............................8.0%

Avobenzone ............................3.0%

Purpose: Sunscreen

Octisalate.................................5.0%

Uses:

- Helps Prevent Sunburn
- If Used as directed with other sun protection measures (see Directions), decreases the risk of skin cancer and early skin aging caused by the sun

Warnings:

For external use only.

Do not use on damaged or broken skin.

When using this product keep out of eyes. Rinse with water to remove.

Stop use and ask a doctor if rash occurs.

Keep out of reach of children. If product is swallowed, get medical help or contact a Poison Control Center right away.

Directions:

- Apply to neck and face before exposure to the sun and the light of day.
- Apply liberally 15 minutes before sun exposure.
- Use a water resistant sunscreen if swimming or sweating, reapply at least every two hours.
- Children under 6 months. Ask a doctor.

USE ONLY AS DIRECTED.

Spending time in the sun increases your risk of skin cancer and early skin aging. To decrease this risk, regularaly use a sunscreen with a Broad Spectrum value of SPF 15 or higher and other sun protection measures including:

- Limit time in the sun, especially from 10 a.m.-2p.m.
- Wear long-sleeved shirts, pants, hats and sunglasses

Inactive Ingredients

Water/Aqua/Eau, Silica, Caprylic/Capric Triglyceride, Glycerin, Xylitylglucoside, Anhydroxylitol, Xylitol, Chondrus Crispus Extract, Sodium Hyaluronate, Glyceryl Stearate, Butyrospermum Parkii (Shea) Butter, Cetearyl Alcohol, Tocopheryl Acetate, Ilex Paraguariensis Leaf Extract, Avena Sativa (Oat) Kernel Extract, Vegetable Collagen, Stearic Acid, Polymethyl Methacrylate, Di-C12-15 Alkyl Fumarate, Cetyl Phosphate, Disodium EDTA, Carbomer, Fragrance, Aminomethyl Propanol, Phenoxyethanol, Caprylyl Glycol, Potassium Sorbate, Hexylene Glycol

PACKAGE LABEL

MADE IN USA OF DOMESTIC AND FOREIGN COMPONENTS

DISTRIBUTED BY:
PROFILE 4 MEN LLC
NAPLES, FL 34108 USA

PROFILE4MEN.COM